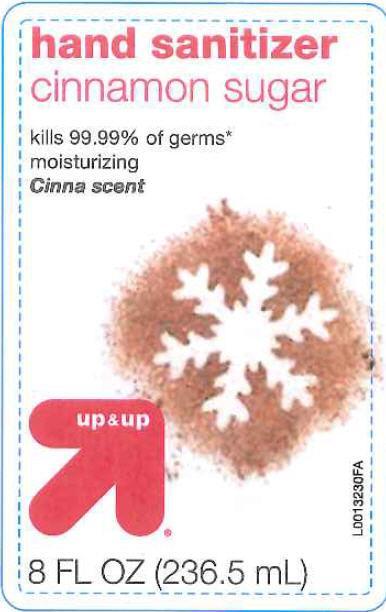 DRUG LABEL: Cinnamon Sugar
NDC: 11673-585 | Form: GEL
Manufacturer: Target Corp.,
Category: otc | Type: HUMAN OTC DRUG LABEL
Date: 20200729

ACTIVE INGREDIENTS: ALCOHOL 558 mg/1 mL
INACTIVE INGREDIENTS: SULISOBENZONE; CARBOMER INTERPOLYMER TYPE A (ALLYL SUCROSE CROSSLINKED); GLYCERIN; ISOPROPYL MYRISTATE; PROPYLENE GLYCOL; FD&C RED NO. 4; D&C RED NO. 33; .ALPHA.-TOCOPHEROL ACETATE; WATER

UP & UP 585

Active ingredients

Active ingredient

Ethyl Alcohol 62%

Purpose

Antiseptic

Uses

- to decrease bacteria on the skin that could cause disease
- recommended for repeated use

Warnings

For external use only-hands

Flammable

Flammable. Keep away from heat and flame.

When using this product

- keep out of eyes. In case of contact with eyes, flush thoroughly with water
- avoid contact with broken skin
- do not inhale or ingest

Stop use

Stop use and ask a doctor if skin irritation develops

Keep out of reach of children. If swallowed, get medical help or contact a Poison Control Center right away.

Directions

- wet hands thoroughly with product and allow to dry without wiping
- for children under 6, use only under adult supervision
- not recommended for infants

Other information

- 2.2ex0em2.2ex0emdo not store above 105°F
- 2.2ex0em2.2ex0emmay discolor some fabrics
- 2.2ex0em2.2ex0emharmful to wood finishes and plastics

Inactive ingredients

Inactive ingredients benzophenon-4, carbomer, fragrance, glycerin, isopropl myristate, propylene, glycol, red 4, red 33, tocopheryl acetate, water

Questions

Questions? Call 1-800-910-6874

claims

Effective at eliminating 99.99% of many common harmful germs and bacteria in as little as 15 seconds

Made in USA with US and foreign components

Adverse Reactions Section

Distributed by Target Corp., MPLS MN 55403

Shop Target.com

principal display panel

hand sanitizer

cinnamon sugar

kills 99.99% of germs

moisturizing

Cinna scent

UP + UP

8 FL OZ (236.5 mL)